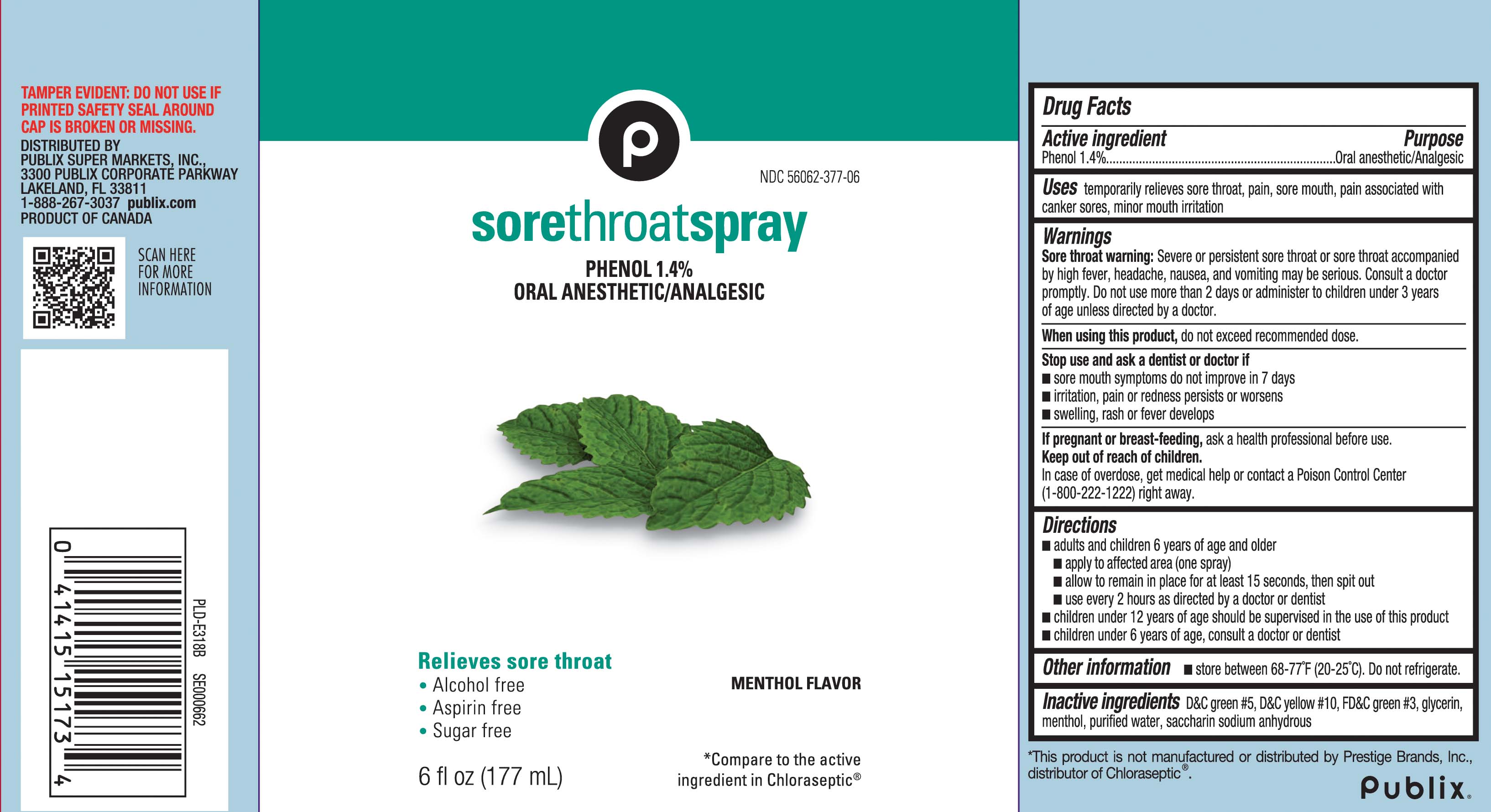 DRUG LABEL: Sore Throat
NDC: 56062-377 | Form: SPRAY
Manufacturer: Publix Supermarkets, Inc.
Category: otc | Type: HUMAN OTC DRUG LABEL
Date: 20250711

ACTIVE INGREDIENTS: PHENOL 1.4 g/100 mL
INACTIVE INGREDIENTS: D&C GREEN NO. 5; GLYCERIN; WATER; SACCHARIN SODIUM; D&C YELLOW NO. 10; FD&C GREEN NO. 3; MENTHOL

Drug Facts

Active ingredient

Phenol 1.4%

Purpose

Oral Anesthetic/Analgesic

Uses

temporarily relieves sore throat, pain, sore mouth, pain associated with canker sores, minor mouth irritation

Warnings

Sore throat warning: Severe or persistent sore throat or sore throat accompanied by high fever, headache, nausea, and vomiting may be serious. Consult a doctor promptly. Do not use more than 2 days or adminster to children under 3 years of age unless directed by a doctor.

When using this product,

do not exceed recommended dose.

Stop use and ask a dentist or doctor if

- sore mouth symptoms do not improve in 7 days
- irritation, pain or redness persists or worsens
- swelling, rash or fever develops

If pregnant or breast-feeding,

ask a health professional before use.

Keep out of reach of children.

In case of overdose, get medical help or contact a Poison Control Center (1-800-222-1222) right away.

Directions

- adults and children 6 years of age and older
  - apply to affected area (one Spray)
  - allow to remain in place for at least 15 second, then spit out
  - use every 2 hours as directed by a doctor or dentist
- children under 12 years of age should be supervised in the use of this product
- children under 6 years of age, consult a doctor or dentist

Other information

- store between 68-77ºF (20-25ºC). Do not refrigerate.

Inactive ingredients

D&C green #5, D&C yellow #10, FD&C green #3, glycerin, menthol, purified water, saccharin sodium anhydrous

Principal Display Panel

*Compare to the active ingredient in Chloraseptic®

Sore Throat Spray

PHENOL 1.4%

ORAL ANESTHETIC/ANALGESIC

Relieves sore throat

- Alcohol free
- Aspirin free
- Sugar free

MENTHOL FLAVOR

FL OZ (mL)

*This product is not manufactured or distributed by Prestige Brands, Inc., distributor of Chloraseptic®.

TAMPER EVIDENT: DO NOT USE IF PRINTED SAFETY SEAL AROUND CAP IS BROKEN OR MISSING.

DISTRIBUTED BY

PUBLIX SUPER MARKETS, INC.

3300 PUBLIX CORPORATE PARKWAY

LAKELAND, FL 33811

publix.com 1-888-267-3037

Package Label

PUBLIX Sore Throat Spray